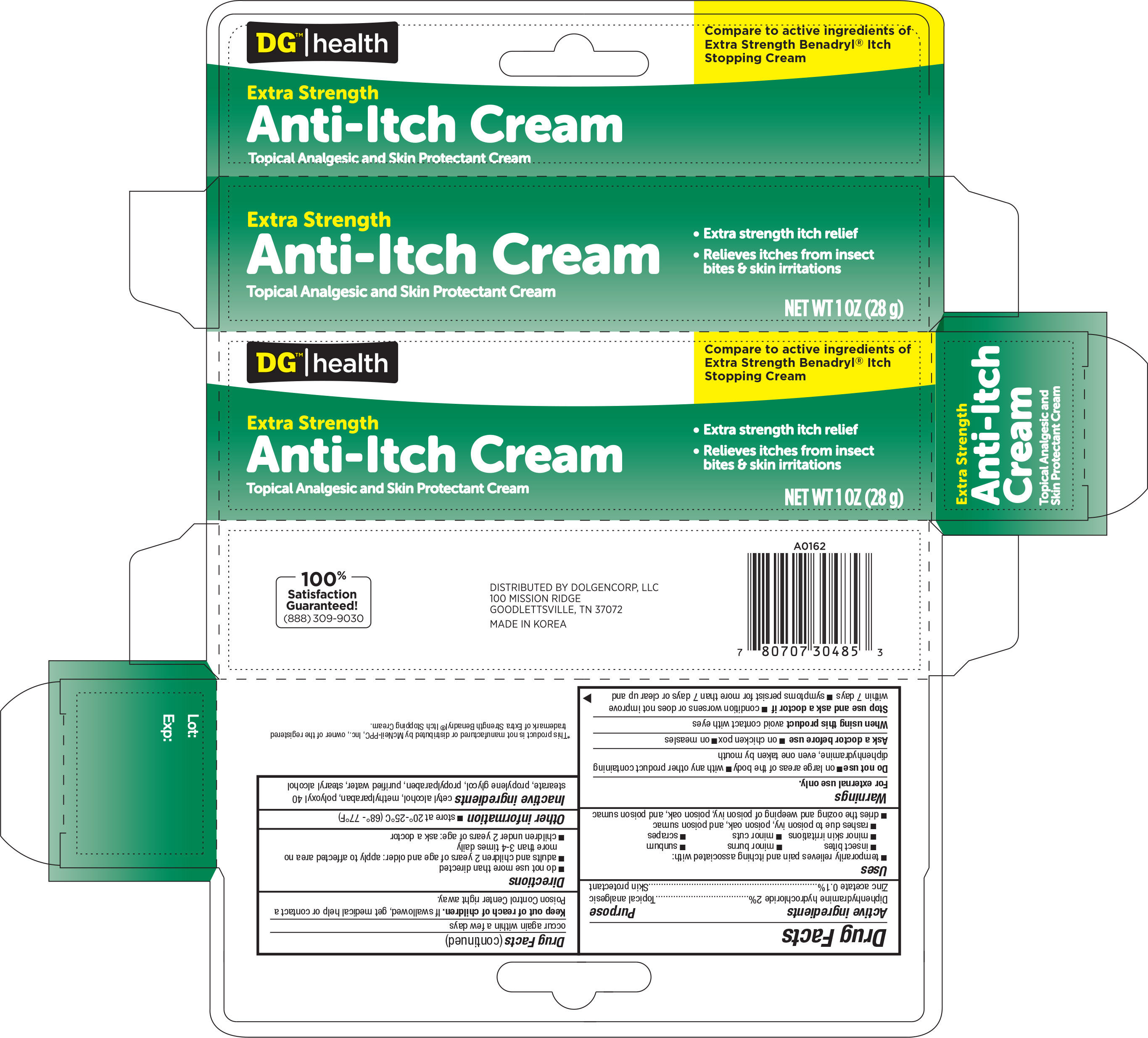 DRUG LABEL: DG HEALTH ANTI ITCH
NDC: 55910-305 | Form: CREAM
Manufacturer: DOLGENCORP, INC.
Category: otc | Type: HUMAN OTC DRUG LABEL
Date: 20160914

ACTIVE INGREDIENTS: DIPHENHYDRAMINE HYDROCHLORIDE 20 mg/1 g; ZINC ACETATE 1 mg/1 g
INACTIVE INGREDIENTS: CETYL ALCOHOL; METHYLPARABEN; POLYOXYL 40 STEARATE; PROPYLENE GLYCOL; PROPYLPARABEN; WATER; STEARYL ALCOHOL

Active ingredients Purpose

Diphenhydramine Hydrochloride 2% ............................................Topical analgesic

Zinc acetate 0.1% .....................................................................Skin protectant

Uses

temporarily relieves pain and itching associated with:

- insect bites
- minor burns
- sunburn
- minor skin irritations
- minor cuts
- scrapes
- rashes due to poison ivy, poison oak and poison sumac
- dries the oozing and weeping of poison ivy, poison oak and poison sumac

Warnings

For external use only

Do not use

- on large areas of the body
- with any other product containing diphenhydramine, even one taken by mouth

Ask a doctor before use

- on chicken pox
- on measles

When using this product

- avoid contact with the eyes

Stop use and ask a doctor if

- condition worsens or does not improve within 7 days
- symptoms persist for more than 7 days or clear up and occur again within a few days

Keep out of reach of children. If swallowed, get medical help or contact a Poison Control Center right away

Directions

- do not use more than directed
- adults and children 2 years of age and older: apply to affected area no more than 3-4 times daily
- children under 2 years of age: ask a doctor

Other information

- store at 20o to 25oC (68o-77oF)

Inactive ingredients

propylene glycol, cetyl alcohol, polyoxyl 40 stearate, methylparaben, propylparaben, purified water.

DOSAGE AND ADMINISTRATION

Distributed By

Dolgencorp, LLC

100 Mission Ridge

Goodlettsville, TN 37072

Made in Korea